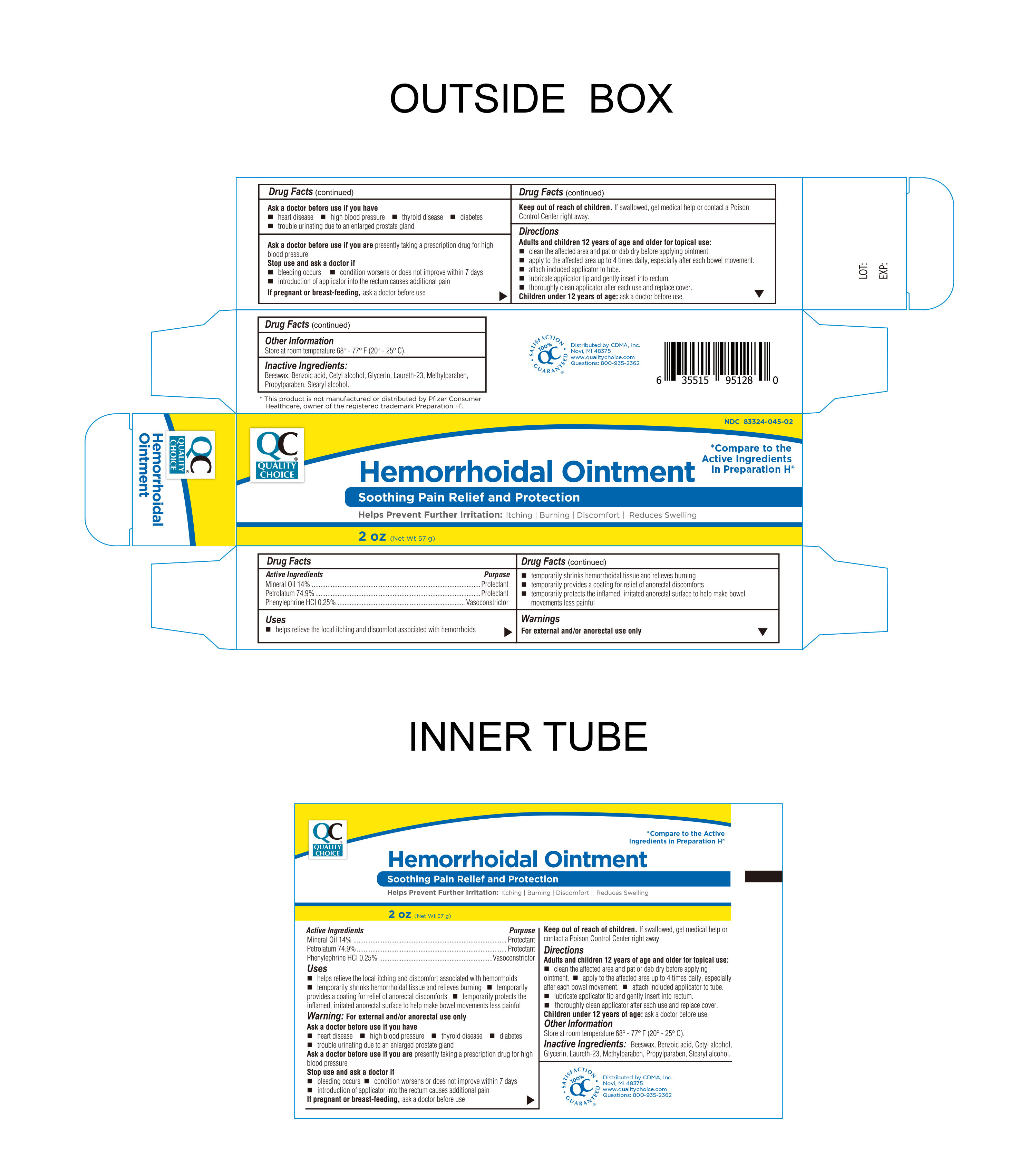 DRUG LABEL: Hemorrhoidal
NDC: 83324-045 | Form: OINTMENT
Manufacturer: Chain Drug Marketing Association Inc.
Category: otc | Type: HUMAN OTC DRUG LABEL
Date: 20250109

ACTIVE INGREDIENTS: PHENYLEPHRINE HYDROCHLORIDE 0.25 g/100 g; MINERAL OIL 14 g/100 g; PETROLATUM 74.9 g/100 g
INACTIVE INGREDIENTS: STEARYL ALCOHOL; BENZOIC ACID; CETYL ALCOHOL; LAURETH-23; METHYLPARABEN; YELLOW WAX; GLYCERIN; PROPYLPARABEN

Quality Choice Hemorrhoidal Ointment

Active Ingredient

Phenylephrine HCI 0.25%

Purpose

Vasoconstrictor

Active Ingredient

Mineral Oil 14%

Purpose

Protectant

Active Ingredient

Petrolatum 74.9%

Purpose

Protectant

Uses

- Helps relieve the local itching and discomfort associated with hemorrhoids
- Temporarily shrinks hemorrhoidal tissue and relieves burning
- Temporarily provides a coating for relief of anorectal discomforts
- Temporarily protects the inflamed, irritated anorectal surface to help make bowel movements less painful

Warnings

For external and/or intrarectal use only

Ask doctor before use if you have

heart disease

high blood pressure

thyroid disease

diabetes

trouble urinating due to an enlarged prostate gland

Ask doctor before use if you arepresently taking a prescription drug for high blood pressure.

Stop Use and Ask Doctor if

- Bleeding occurs
- Condition worsens or does not improve within 7 days
- Introduction of applicator into the rectum causes additional pain

If Pregnant or breast-feeding

Ask a doctor before use

Keep out of reach of children

If swallowed get medical help or contact a Poison Control Center right away.

Ask doctor before use if you are presently taking a prescription drug for high blood pressure.

Ask doctor before use if you have:

- heart disease
- high blood pressure
- thyroid disease
- diabetes
- trouble urinating due to an enlarged prostate gland

Directions

- Adults and children 12 years of age and older for topical use:
- Clean the affected area and pat or dab dry before applying ointment.
- apply to the affected area up to 4 times daily, especially after each bowel movement.
- attach included applicator to tube
- lubricate applicator tip and gently insert into the rectum.
- thoroughly clean applicator after each use and replace cover.
- Children under 12 years of age; ask doctor before use

Other Information

- Store at room temperature 20º-25ºC (68º-77ºF)

Inactive Ingredients

Beeswax, Benzoic Acid, Cetyl alcohol, Glycerin, Methylparaben, Laureth-23, Propylparaben, Stearyl alcohol

Questions or Comments?

1-800-935-2362

Distributed By

Distributed By CDMA Inc.

43157 W 9 Mile Road

Novi, MI 48375

www.qualitychoice.com

Questions: 800-935-2362

Product of PRC

This product is not manufactured or distributed by Pfizer Consumer Healthcare, owner of the registered trademark Preparation H.